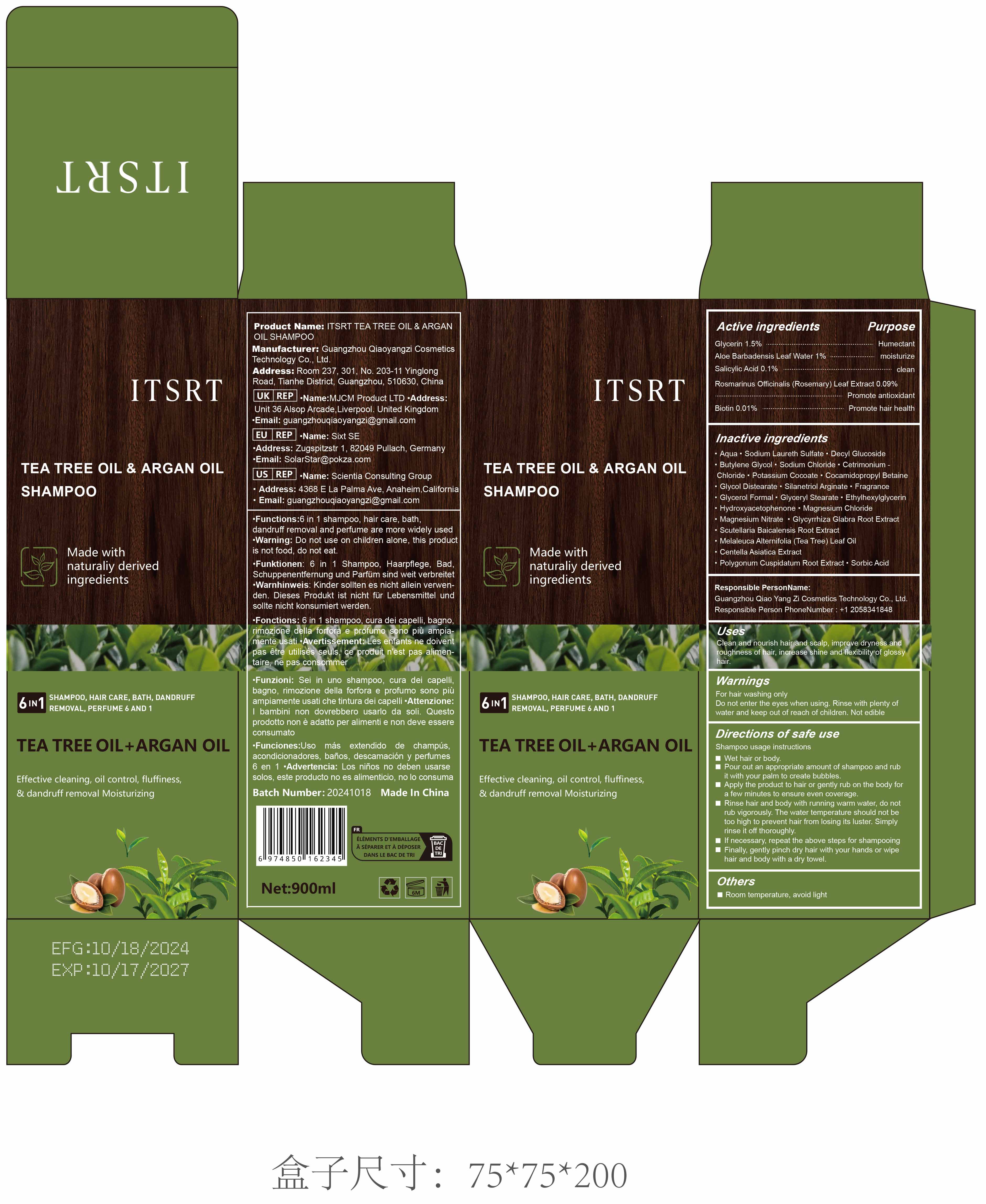 DRUG LABEL: ITSRT Tea Tree Oil and Argan Oil
NDC: 84751-097 | Form: EMULSION
Manufacturer: Guangzhou Qiaoyangzi Cosmetics Technology Co Ltd
Category: otc | Type: HUMAN OTC DRUG LABEL
Date: 20241219

ACTIVE INGREDIENTS: ALOE VERA LEAF 0.1 mg/500 mL; BIOTIN 0.01 mg/500 mL; ROSEMARY 0.009 mg/500 mL; SORBIC ACID 0.03 mg/500 mL; GLYCERIN 0.15 mg/500 mL
INACTIVE INGREDIENTS: AQUA 7.165 mg/500 mL

Active ingredients

Glycerin 1.500%
Aloe Barbadensis Leaf Water 1.000%
Sorbic Acid 0.300%
Rosmarinus Officinalis (Rosemary) Leaf Extract 0.09%
Biotin 0.01%

INACTIVE INGREDIENT SECTION

Aqua 71.650%
Sodium Laureth Sulfate 8.300%
Decyl Glucoside 2.000%
Butylene Glycol 2.000%
Sodium Chloride 1.750%
Cetrimonium Chloride 1.650%
Potassium Cocoate 1.500%
Cocamidopropyl Betaine 1.500%
Glycol Distearate 1.000%
Silanetriol Arginate 1.000%
Fragrance 0.500%
Glycerol Formal 0.500%
Glyceryl Stearate 0.500%
Ethylhexylglycerin 0.500%
Hydroxyacetophenone 0.350%
Magnesium Chloride 0.100%
Magnesium Nitrate 0.100%
Glycyrrhiza Glabra Root Extract 0.30%
Scutellaria Baicalensis Root Extract 0.30%
Salicylic Acid 0.10%
Melaleuca Alternifolia (Tea Tree) Leaf Oil 0.05%
Centella Asiatica Extract 0.05%
Polygonum Cuspidatum Root Extract 0.05%

Purpose

Cleansing: Removes dirt, oil, and buildup from hair and scalp.
Moisturizing: Helps to hydrate and retain moisture in hair.
Soothing: Relieves scalp irritation and discomfort.
Antioxidant Protection: Provides protection against environmental damage.
Promotes Hair Health: Strengthens and nourishes hair to promote healthy growth.
Exfoliation: Helps to gently exfoliate the scalp to reduce flakiness and buildup.

Uses

Indications & Usage:
This shampoo is indicated for:

Cleansing the hair and scalp: Effectively removes dirt, excess oil, and product buildup.
Moisturizing and hydrating: Helps maintain the moisture balance of the hair and scalp, leaving hair soft and nourished.
Soothe irritated or sensitive scalps: Soothes the scalp to reduce itching, dryness, and inflammation.
Promoting hair health: Strengthens hair, supports healthy growth, and helps reduce hair breakage.
Preventing and treating dandruff: Gently exfoliates the scalp to remove dead skin cells, reducing flakiness and preventing dandruff.
Providing antioxidant protection: Protects the scalp and hair from damage caused by environmental stressors.

Warnings

For external use only.
Avoid contact with eyes. In case of contact, rinse immediately with plenty of water. If irritation persists, consult a healthcare professional.
Do not swallow. If swallowed, seek medical advice immediately or contact a Poison Control Center.
If irritation or redness develops, discontinue use immediately and consult a healthcare provider. This includes any signs of scalp sensitivity, such as itching, burning, or rash.
Keep out of reach of children. In case of accidental ingestion, seek medical help right away.
Do not use if you are allergic to any ingredients listed. If you are unsure, perform a patch test before full use.
Patch Test Instructions: Apply a small amount of product to the inside of your elbow or behind your ear and wait 24 hours. If irritation, redness, or swelling occurs, do not use the product.
Use only as directed. Overuse or misuse may lead to scalp dryness or irritation.
Use caution if you have a sensitive scalp or skin. Some active ingredients (e.g., Tea Tree Oil, Salicylic Acid) may cause mild irritation for those with extremely sensitive skin.
If pregnant or breastfeeding, consult a healthcare provider before use to ensure the safety of the product for you and your baby.
Keep the cap tightly closed to prevent contamination. Store in a cool, dry place, away from excessive heat or sunlight.

Stop use

Stop Use and Consult a Doctor If:
Irritation or redness develops on the scalp or skin, including symptoms like itching, burning, or swelling.
Severe or persistent scalp irritation occurs after use, such as a rash, blistering, or open sores.
Eyes become irritated after accidental contact with the shampoo. If irritation persists, seek medical advice.
Condition worsens or does not improve after using the product regularly.
Allergic reactions occur, such as hives, difficulty breathing, or swelling of the face, lips, or tongue.
Excessive dryness or flakiness of the scalp is noticed after use. If this occurs, reduce the frequency of use or discontinue use and consult a healthcare provider.

Do not use

Stop Use and Consult a Doctor If:
Irritation or redness develops on the scalp or skin, including symptoms like itching, burning, or swelling.
Severe or persistent scalp irritation occurs after use, such as a rash, blistering, or open sores.
Eyes become irritated after accidental contact with the shampoo. If irritation persists, seek medical advice.
Condition worsens or does not improve after using the product regularly.
Allergic reactions occur, such as hives, difficulty breathing, or swelling of the face, lips, or tongue.
Excessive dryness or flakiness of the scalp is noticed after use. If this occurs, reduce the frequency of use or discontinue use and consult a healthcare provider.

Keep out of reach of children!

Rationale:
Accidental ingestion: The presence of ingredients like Tea Tree Oil, Salicylic Acid, and other active botanicals can be harmful if ingested in large amounts. If a child accidentally swallows the shampoo, it may cause gastrointestinal discomfort or other symptoms.
Children under 2 years of age: Young children have more sensitive skin and are more susceptible to irritation or adverse reactions from certain active ingredients like Tea Tree Oil and Salicylic Acid. It is important to consult a healthcare provider before using such products on children under 2.
General safety: Since this is a topical product, it's always essential to keep it out of reach of children to avoid any potential misuse or accidental exposure.

Precautions for Use

When Using This Product:
Avoid contact with eyes. If contact occurs, rinse eyes thoroughly with water. If irritation persists, seek medical attention.
Do not ingest. If swallowed, contact a Poison Control Center or seek medical help immediately.
Use only as directed. Excessive use or misuse may cause scalp dryness or irritation.
If irritation or redness occurs, discontinue use immediately and consult a healthcare provider. This includes itching, burning, or rash on the scalp.
Keep out of reach of children. In case of accidental ingestion, seek medical advice immediately.
For external use only. Do not apply to open wounds or broken skin.
Use with caution if you have sensitive skin. Some ingredients, such as Tea Tree Oil or Salicylic Acid, may cause irritation in individuals with particularly sensitive skin or scalp.
Do not use more frequently than recommended. Overuse may lead to dryness or scalp irritation.
Avoid applying to irritated or damaged skin. Use only on healthy, intact scalp and hair.

Instructions for Use

Wet hair thoroughly with lukewarm water.
Apply a generous amount of shampoo to your palm. The amount may vary depending on hair length and thickness.
Massage gently into the scalp and hair, working the shampoo through to the ends. Use your fingertips (not nails) to massage the scalp in circular motions to create a rich lather.
Leave the shampoo on the scalp for 1-2 minutes to allow the active ingredients to work.
Rinse thoroughly with lukewarm water, ensuring all shampoo is removed from the hair and scalp.
For best results, follow with a conditioner that suits your hair type to lock in moisture and enhance the shampoo’s benefits.
Use regularly for optimal results. For daily use, adjust frequency based on your scalp and hair type. If you have a dry scalp, consider using it every other day or as needed.

DOSAGE & ADMINISTRATION SECTION

Dosage & Administration:
Amount to Use:
Dispense a quarter-sized amount (approximately 5–10 mL) of shampoo onto your palm. The exact amount may vary depending on your hair length, thickness, and personal preference.
Frequency of Use:
For normal to oily hair/scalp: Use the shampoo 1 to 2 times per week or as needed to cleanse and refresh the scalp and hair.
For dry or sensitive scalp: Use the shampoo every other day or 2-3 times a week to avoid over-drying the scalp.
For dandruff or scalp issues: Use the shampoo 2-3 times per week or as directed by a healthcare provider.
How to Apply:
Wet hair thoroughly before applying the shampoo.
Massage gently into the scalp and hair, working the product through to the ends of the hair.
Allow the shampoo to sit for 1-2 minutes to let the active ingredients work, especially for exfoliating or soothing effects.
Rinse thoroughly with water.
Follow-Up: For best results, follow with a conditioner that suits your hair type to lock in moisture and maintain scalp health.